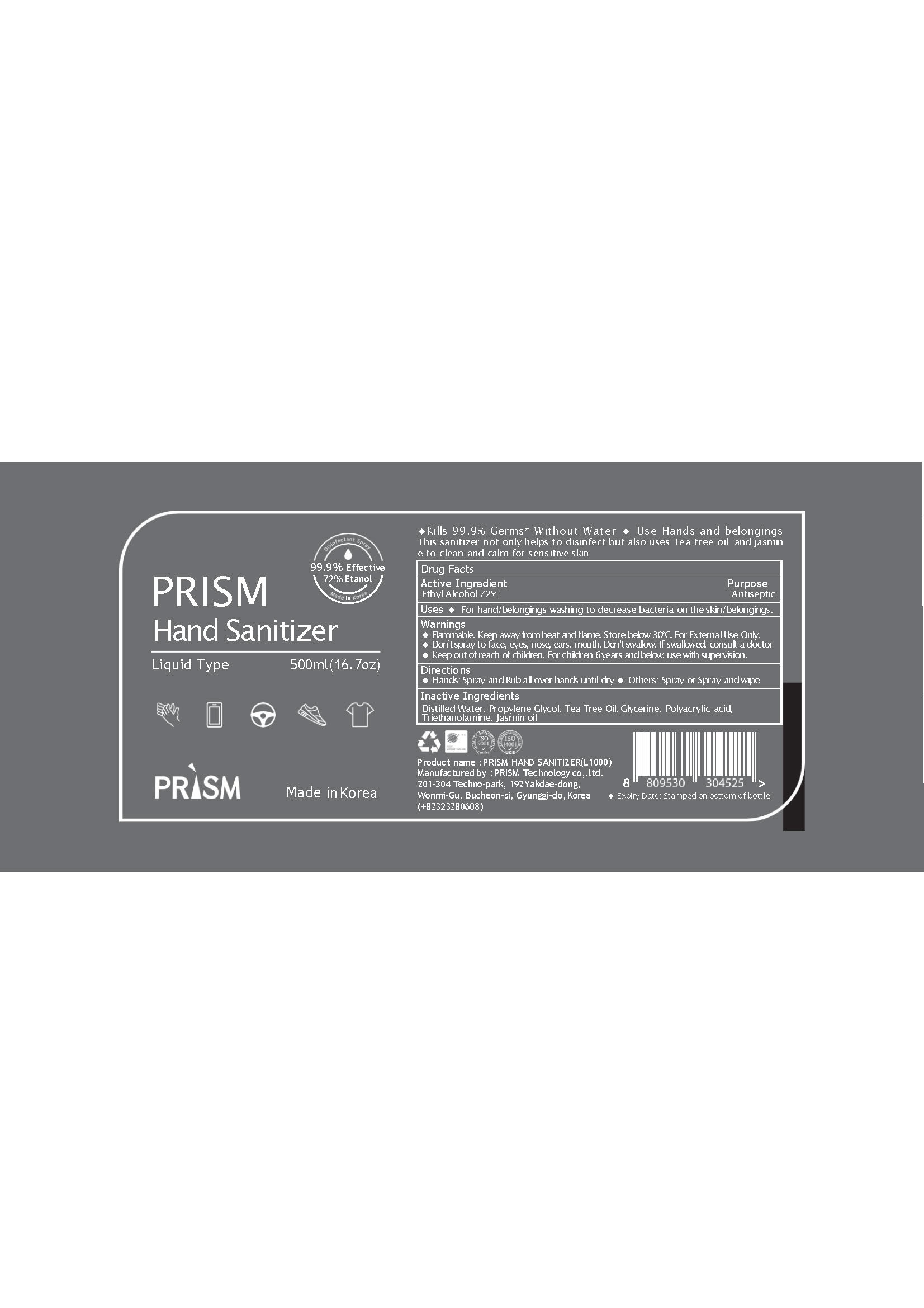 DRUG LABEL: PRISM Hand Sanitizer L1000
NDC: 79554-0002 | Form: LIQUID
Manufacturer: Prism Technology
Category: otc | Type: HUMAN OTC DRUG LABEL
Date: 20200711

ACTIVE INGREDIENTS: ALCOHOL 72 mL/100 mL
INACTIVE INGREDIENTS: TROLAMINE; PROPYLENE GLYCOL; CARBOMER 940; GLYCERIN; JASMINUM OFFICINALE FLOWER; TEA TREE OIL

Active Ingredient(s)

alcohol

Purpose

hand sanitizer

Use

spray and rub all over hands until dry

spray or spray and wipe

Warnings

For external use only.
Flammable, keep away from fire or flame.
When using this product, avoid contact with the eyes. In case of contact, rinse eyes thoroughly with water.
Stop use and ask a doctor if irritation or redness appears and lasts.

 Keep out of reach of children. If swallowed, get medical help or contact a Poison Control Center immediately.

Directions

for external use only

INACTIVE INGREDIENT

Water
Propylene Glycol
Glycerine
Carbomer
Triethanol amine
Tea Tree Oil
Jasmin Oil